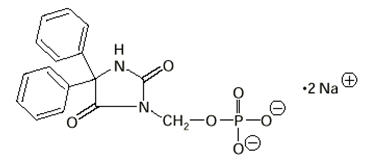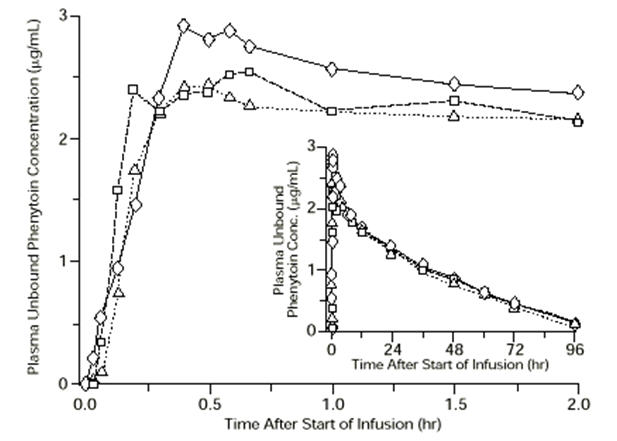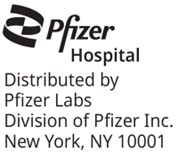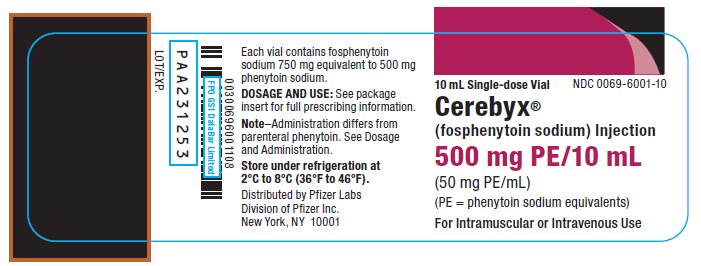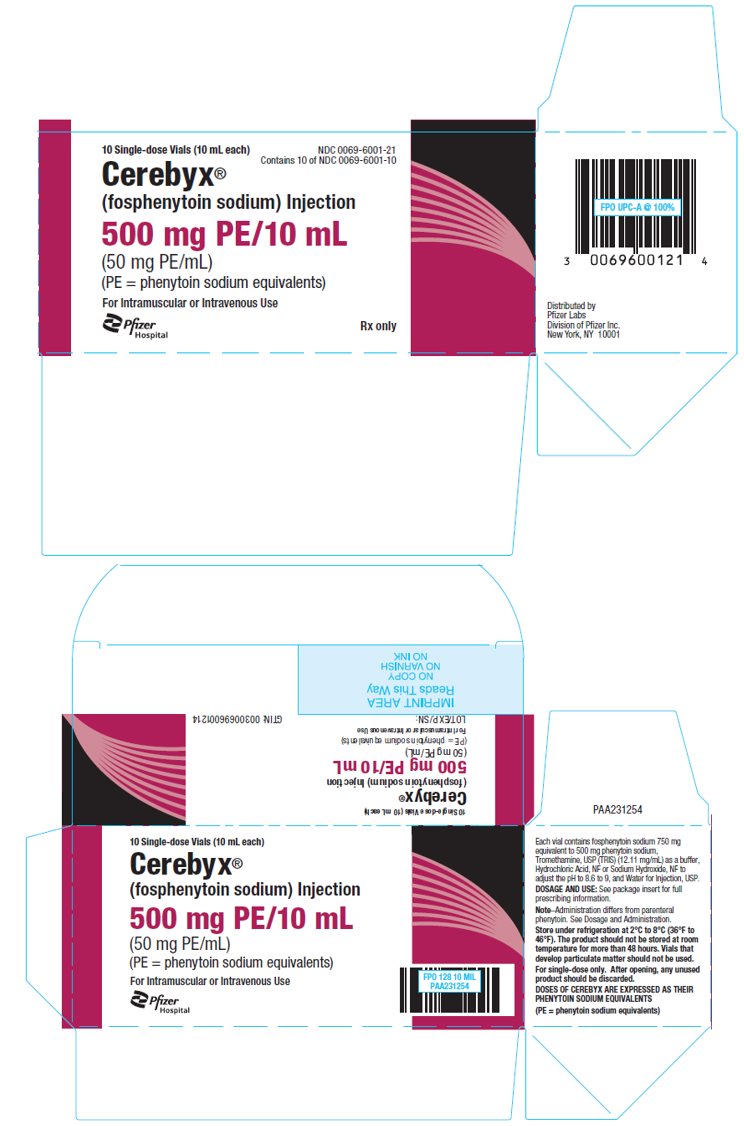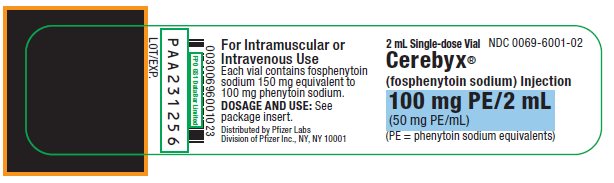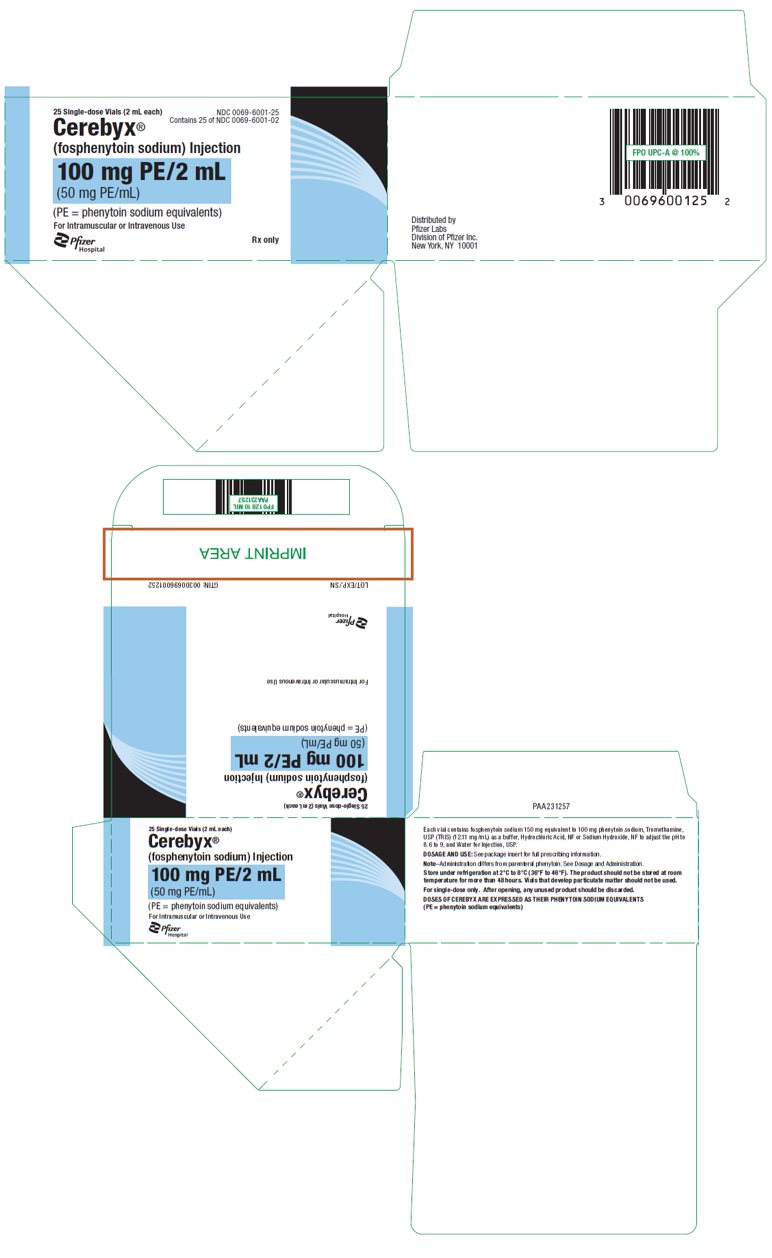 DRUG LABEL: CEREBYX
NDC: 0069-6001 | Form: INJECTION, SOLUTION
Manufacturer: Pfizer Laboratories Div Pfizer Inc
Category: prescription | Type: HUMAN PRESCRIPTION DRUG LABEL
Date: 20250828

ACTIVE INGREDIENTS: FOSPHENYTOIN SODIUM 50 mg/1 mL
INACTIVE INGREDIENTS: WATER; TROMETHAMINE; HYDROCHLORIC ACID; SODIUM HYDROXIDE

HIGHLIGHTS OF PRESCRIBING INFORMATION

These highlights do not include all the information needed to use CEREBYX® safely and effectively. See full prescribing information for CEREBYX®.
CEREBYX® (fosphenytoin sodium) injection, for intravenous or intramuscular use
Initial U.S. Approval: 1996

WARNING: CARDIOVASCULAR RISK ASSOCIATED WITH RAPID INFUSION RATES

See full prescribing information for complete boxed warning.

- The rate of intravenous CEREBYX administration should not exceed 150 mg phenytoin sodium equivalents (PE) per minute in adults and 2 mg PE/kg/min (or 150 mg PE/min, whichever is slower) in pediatric patients because of the risk of severe hypotension and cardiac arrhythmias.
- Careful cardiac monitoring is needed during and after administering intravenous CEREBYX.
- Reduction in rate of administration or discontinuation of dosing may be needed (2.3, 2.4, 5.2).

1 INDICATIONS AND USAGE

CEREBYX is indicated for the treatment of generalized tonic-clonic status epilepticus and prevention and treatment of seizures occurring during neurosurgery. CEREBYX can also be substituted, as short-term use, for oral phenytoin. CEREBYX should be used only when oral phenytoin administration is not possible. (1)

2 DOSAGE AND ADMINISTRATION

- The dose, concentration, and infusion rate of CEREBYX should always be expressed as phenytoin sodium equivalents (PE) (2.1)
- For Status Epilepticus:
  - Adult loading dose is 15 to 20 mg PE/kg at a rate of 100 to 150 mg PE/min (2.3)
  - Pediatric loading dose is 15 to 20 mg PE/kg at a rate of 2 mg PE/kg/min (or 150 mg PE/min, whichever is slower) (2.3)
- For Non-emergent Loading and Maintenance Dosing:
  - Adult loading dose is 10 to 20 mg PE/kg given IV or IM; initial maintenance dose is 4 to 6 mg PE/kg/day in divided doses (2.4)
  - Pediatric loading dose is 10 to 15 mg PE/kg at a rate of 1 to 2 mg PE/kg/min (or 150 mg PE/min, whichever is slower); initial maintenance dose is 2 to 4 mg PE/kg every 12 hours at a rate of 1 to 2 mg PE/kg/min (or 100 mg PE/min, whichever is slower) (2.4)
- Intramuscular Administration:
  - CEREBYX should ordinarily not be given intramuscularly (2.3, 2.4)

3 DOSAGE FORMS AND STRENGTHS

Injection: 50 mg phenytoin sodium equivalents (PE)/mL available as:

- 10 mL single-dose injection vials, each containing 500 mg PE/10 mL (50 mg PE/mL) (3)
- 2 mL single-dose injection vials, each containing 100 mg PE/2 mL (50 mg PE/mL) (3)

4 CONTRAINDICATIONS

- Hypersensitivity to CEREBYX, its ingredients, phenytoin, hydantoins (4)
- Sinus bradycardia, sino-atrial block, second and third degree A-V block, and Adams-Stokes syndrome (4)
- A history of prior acute hepatotoxicity attributable to CEREBYX or phenytoin (4, 5.8)
- Coadministration with delavirdine (4)

5 WARNINGS AND PRECAUTIONS

- Dosing Errors: Do not confuse the amount of drug to be given in PE with the concentration of the drug in the vial. Ensure the appropriate volume is withdrawn from the vial when preparing for administration. (5.1)
- Withdrawal Precipitated Seizure: May precipitate status epilepticus. Dose reductions or discontinuation should be done gradually. (5.3)
- Serious Dermatologic Reactions: Discontinue at the first sign of a rash, unless clearly not drug-related. If signs or symptoms suggest SJS/TEN, CEREBYX should not be resumed; consider alternative therapy. (5.4)
- Drug Reaction with Eosinophilia and Systemic Symptoms (DRESS)/Multiorgan Hypersensitivity: If signs or symptoms of hypersensitivity are present, evaluate the patient immediately. Discontinue if an alternative etiology cannot be established. (5.5)
- Angioedema: Discontinue immediately if symptoms of angioedema such as facial, perioral, or upper airway swelling occur. (5.7)
- Hematopoietic Complications: If occurs, follow-up observation is indicated and an alternative antiepileptic treatment should be used. (5.9)

6 ADVERSE REACTIONS

Most common adverse reactions (incidence ≥10%) are:

- Adults: pruritus, nystagmus, dizziness, somnolence, and ataxia
- Pediatrics: vomiting, nystagmus, and ataxia (6.1)

To report SUSPECTED ADVERSE REACTIONS, contact Pfizer, Inc. at 1-800-438-1985 or FDA at 1-800-FDA-1088 or www.fda.gov/medwatch.

7 DRUG INTERACTIONS

- Multiple drug interactions because of extensive plasma protein binding, saturable metabolism, and potent induction of hepatic enzymes (7.1, 7.2)

8 USE IN SPECIFIC POPULATIONS

- Pregnancy: Phenytoin (the active metabolite of CEREBYX) prenatal exposure may increase risks for congenital malformations and other adverse developmental outcomes (5.15, 8.1)
- Renal and/or Hepatic Impairment or Hypoalbuminemia: Monitor unbound phenytoin concentrations in these patients (8.6)

FULL PRESCRIBING INFORMATION

WARNING: CARDIOVASCULAR RISK ASSOCIATED WITH RAPID INFUSION RATES

The rate of intravenous CEREBYX administration should not exceed 150 mg phenytoin sodium equivalents (PE) per minute in adults and 2 mg PE/kg/min (or 150 mg PE/min, whichever is slower) in pediatric patients because of the risk of severe hypotension and cardiac arrhythmias. Careful cardiac monitoring is needed during and after administering intravenous CEREBYX. Although the risk of cardiovascular toxicity increases with infusion rates above the recommended infusion rate, these events have also been reported at or below the recommended infusion rate. Reduction in rate of administration or discontinuation of dosing may be needed [see Dosage and Administration (2.3, 2.4) and Warnings and Precautions (5.2)].

1 INDICATIONS AND USAGE

CEREBYX is indicated for the treatment of generalized tonic-clonic status epilepticus and prevention and treatment of seizures occurring during neurosurgery. CEREBYX can also be substituted, short-term, for oral phenytoin. CEREBYX should be used only when oral phenytoin administration is not possible [see Dosage and Administration (2.4) and Warnings and Precautions (5.2)].

2 DOSAGE AND ADMINISTRATION

2.1 Important Administration Instructions to Avoid Dosing Errors

Use caution when administering CEREBYX because of the risk of dosing errors [see Warnings and Precautions (5.1)].

Phenytoin Sodium Equivalents (PE)

The dose, concentration, and infusion rate of CEREBYX should always be expressed as phenytoin sodium equivalents (PE). There is no need to perform molecular weight-based adjustments when converting between fosphenytoin and phenytoin sodium doses. CEREBYX should always be prescribed and dispensed in phenytoin sodium equivalent units (PE). The amount and concentration of fosphenytoin is always expressed in terms of mg of phenytoin sodium equivalents (mg PE).

Concentration of 50 mg PE/mL

Do not confuse the concentration of CEREBYX with the total amount of drug in the vial.

Errors, including fatal overdoses, have occurred when the concentration of the vial (50 mg PE/mL) was misinterpreted to mean that the total content of the vial was 50 mg PE. These errors have resulted in two- or ten-fold overdoses of CEREBYX since each of the vials actually contains a total of 100 mg PE (2 mL vial) or 500 mg PE (10 mL vial). Ensure the appropriate volume of CEREBYX is withdrawn from the vial when preparing the dose for administration. Attention to these details may prevent some CEREBYX medication errors from occurring.

2.2 Preparation

Prior to intravenous (IV) infusion, dilute CEREBYX in 5% Dextrose Injection or 0.9% Sodium Chloride Injection to a concentration ranging from 1.5 to 25 mg PE/mL. The maximum concentration of CEREBYX in any solution should be 25 mg PE/mL. When CEREBYX is given as an IV infusion, CEREBYX needs to be diluted and should only be administered at a rate not exceeding 150 mg PE/min.

Parenteral drug products should be inspected visually for particulate matter and discoloration prior to administration, whenever solution and container permit.

For single-dose only. After opening, any unused product should be discarded.

2.3 Status Epilepticus

- Because of the risk of hypotension and cardiac arrhythmias, the rate of administration for IV CEREBYX should be no greater than 150 mg PE/min in adults and 2 mg PE/kg/min (or 150 mg PE/min, whichever is slower) in pediatric patients [see Warnings and Precautions (5.2)]. Continuous monitoring of the electrocardiogram, blood pressure, and respiratory function is essential, and the patient should be observed throughout the period where maximal serum phenytoin concentrations occur, approximately 10 to 20 minutes after the end of CEREBYX infusions.
- Because the full antiepileptic effect of phenytoin, whether given as CEREBYX or parenteral phenytoin, is not immediate, other measures, including concomitant administration of an IV benzodiazepine, will usually be necessary for the control of status epilepticus.
- The loading dose should be followed by maintenance doses of either CEREBYX or phenytoin [see Dosage and Administration (2.4)].
- If administration of CEREBYX does not terminate seizures, the use of other anticonvulsants and other appropriate measures should be considered.

Adult and Pediatric Status Epilepticus Dosing:

Table 1. Status Epilepticus Loading Dosages
Population | Dosage | Infusion rate
Adult | 15 mg PE/kg to 20 mg PE/kg | 100 mg PE/min to 150 mg PE/min, do not exceed a maximum rate of 150 mg PE/min
Pediatric (Birth to less than 17 years of age) | 15 mg PE/kg to 20 mg PE/kg | 2 mg PE/kg/min, or 150 mg PE/min, whichever is slower

Even though loading doses of CEREBYX have been given by the IM route for other indications when IV access is impossible, IM CEREBYX should ordinarily not be used in the treatment of status epilepticus because therapeutic phenytoin concentrations may not be reached as quickly as with IV administration.

Intramuscular administration of CEREBYX should ordinarily not be used in pediatric patients. When IV access has been impossible, loading doses of CEREBYX have been given by the IM route.

2.4 Non-emergent Loading and Maintenance Dosing

- Because of the risk of hypotension and cardiac arrhythmias, the rate of administration for IV CEREBYX should be no greater than 150 mg PE/min in adults. For loading doses in pediatric patients, the rate should not exceed 2 mg PE/kg/min (or 150 mg PE/min, whichever is slower). For maintenance doses in pediatric patients, the rate should not exceed 1 to 2 mg PE/kg/min (or 100 mg PE/min, whichever is slower). Continuous monitoring of the electrocardiogram, blood pressure, and respiratory function is essential, and the patient should be observed throughout the period where maximal serum phenytoin concentrations occur (approximately 10 to 20 minutes after the end of CEREBYX infusions).
- After the initial maintenance dose, subsequent maintenance doses should be individualized by monitoring serum phenytoin concentrations to achieve a target therapeutic concentration of phenytoin [see Dosage and Administration (2.5) and Warnings and Precautions (5.17)].

Adult and Pediatric Non-emergent Loading and Maintenance Dosing:

Table 2. Non-emergent Loading Dosages
Population | Dosage | Infusion rate
Adult | 10 mg PE/kg to 20 mg PE/kg | Not to exceed a maximum rate of 150 mg PE/min
Pediatric (Birth to less than 17 years of age) | 10 mg PE/kg to 15 mg PE/kg | 1 mg PE/kg/min to 2 mg PE/kg/min, or 150 mg PE/min, whichever is slower

Table 3. Maintenance Dosages
Population | Dosage | Infusion rate
Adult | Initial Maintenance Dosage: 4 mg PE/kg/day to 6 mg PE/kg/day in divided doses | Not to exceed a maximum rate of 150 mg PE/min
Pediatric (Birth to less than 17 years of age) | Initial Maintenance Dosage: 2 mg PE/kg to 4 mg PE/kg (dose given 12 hours after the loading dose) | 1 mg PE/kg/min to 2 mg PE/kg/min, or 100 mg PE/min, whichever is slower
Pediatric (Birth to less than 17 years of age) | Maintenance Dosage after Initial Maintenance Dosage: 4 mg PE/kg/day to 8 mg PE/kg/day in divided doses (continued every 12 hours after initial maintenance dose) | 1 mg PE/kg/min to 2 mg PE/kg/min, or 100 mg PE/min, whichever is slower

Because of the risks of cardiac and local toxicity associated with intravenous CEREBYX, oral phenytoin should be used whenever possible. Intramuscular administration of CEREBYX should ordinarily not be used in pediatric patients.

2.5 Laboratory Tests and Monitoring Levels

Laboratory Tests:

CEREBYX (or phenytoin) doses are usually selected to attain therapeutic serum total phenytoin concentrations of 10 to 20 mcg/mL (unbound phenytoin concentrations of 1 to 2 mcg/mL). Following CEREBYX administration, it is recommended that phenytoin concentrations not be monitored until conversion to phenytoin is essentially complete. This occurs within approximately 2 hours after the end of IV infusion and 4 hours after intramuscular (IM) injection. Prior to complete conversion, commonly used immunoanalytical techniques, such as TDx®/TDxFLx™ (fluorescence polarization) and Emit® 2000 (enzyme multiplied), may significantly overestimate serum phenytoin concentrations because of cross-reactivity with fosphenytoin. The error is dependent on serum phenytoin and fosphenytoin concentration (influenced by CEREBYX dose, route and rate of administration, and time of sampling relative to dosing), and analytical method. Chromatographic assay methods accurately quantitate phenytoin concentrations in biological fluids in the presence of fosphenytoin. Prior to complete conversion, blood samples for phenytoin monitoring should be collected in tubes containing EDTA as an anticoagulant to minimize ex vivo conversion of fosphenytoin to phenytoin. However, even with specific assay methods, phenytoin concentrations measured before conversion of fosphenytoin is complete will not reflect phenytoin concentrations ultimately achieved.

Monitoring Levels:

Trough levels provide information about clinically effective serum level range and are obtained just prior to the patient's next scheduled dose. Peak levels indicate an individual's threshold for emergence of dose-related side effects and are obtained at the time of expected peak concentration. Therapeutic effect without clinical signs of toxicity occurs more often with serum total phenytoin concentrations between 10 and 20 mcg/mL (unbound phenytoin concentrations of 1 to 2 mcg/mL), although some mild cases of tonic-clonic (grand mal) epilepsy may be controlled with lower serum levels of phenytoin. In patients with renal or hepatic disease, or in those with hypoalbuminemia, the monitoring of unbound phenytoin concentrations may be more relevant [see Dosage and Administration (2.7)].

2.6 Parenteral Substitution for Oral Phenytoin Therapy

When treatment with oral phenytoin is not possible, CEREBYX can be substituted for oral phenytoin at the same total daily phenytoin sodium equivalents (PE) dose. Dilantin capsules are approximately 90% bioavailable by the oral route. Phenytoin, derived from administration of CEREBYX, is 100% bioavailable by both the IM and IV routes. For this reason, serum phenytoin concentrations may increase modestly when IM or IV CEREBYX is substituted for oral phenytoin sodium therapy. The rate of administration for IV CEREBYX should be no greater than 150 mg PE/min in adults and 2 mg PE/kg/min (or 150 mg PE/min, whichever is slower) in pediatric patients. In controlled trials, IM CEREBYX was administered as a single daily dose utilizing either 1 or 2 injection sites. Some patients may require more frequent dosing. Intramuscular administration of CEREBYX should ordinarily not be used in pediatric patients.

2.7 Dosing in Patients with Renal or Hepatic Impairment or Hypoalbuminemia

Because the fraction of unbound phenytoin (the active metabolite of CEREBYX) is increased in patients with renal or hepatic disease, or in those with hypoalbuminemia, the monitoring of phenytoin serum levels should be based on the unbound fraction in those patients. After IV CEREBYX administration to patients with renal and/or hepatic disease, or in those with hypoalbuminemia, fosphenytoin clearance to phenytoin may be increased without a similar increase in phenytoin clearance. This has the potential to increase the frequency and severity of adverse events [see Warnings and Precautions (5.13)].

2.8 Dosing in Geriatrics

The clearance of phenytoin (the active metabolite of CEREBYX) is decreased slightly in elderly patients and lower or less frequent dosing may be required [see Clinical Pharmacology (12.3)].

2.9 Dosing during Pregnancy

Decreased serum concentrations of phenytoin (the active metabolite of CEREBYX) may occur during pregnancy because of altered phenytoin pharmacokinetics [see Clinical Pharmacology (12.3)]. Periodic measurement of serum phenytoin concentrations should be performed during pregnancy, and the CEREBYX dosage should be adjusted as necessary. Postpartum restoration of the original dosage will probably be indicated [see Use in Specific Populations (8.1)]. Because of potential changes in protein binding during pregnancy, the monitoring of phenytoin serum levels should be based on the unbound fraction.

3 DOSAGE FORMS AND STRENGTHS

CEREBYX Injection is a clear, colorless to pale yellow solution available as 50 mg phenytoin sodium equivalents (PE) per mL in:

- 10 mL single-dose injection vials, each containing 500 mg PE/10 mL (50 mg PE/mL)
- 2 mL single-dose injection vials, each containing 100 mg PE/2 mL (50 mg PE/mL)

4 CONTRAINDICATIONS

CEREBYX is contraindicated in patients with:

- A history of hypersensitivity to CEREBYX or its inactive ingredients, or to phenytoin or other hydantoins [see Warnings and Precautions (5.6)]. Reactions have included angioedema.
- Sinus bradycardia, sino-atrial block, second and third degree A-V block, or Adams-Stokes syndrome because of the effect of parenteral phenytoin or CEREBYX on ventricular automaticity.
- A history of prior acute hepatotoxicity attributable to CEREBYX or phenytoin [see Warnings and Precautions (5.8)].
- Coadministration with delavirdine because of the potential for loss of virologic response and possible resistance to delavirdine or to the class of non-nucleoside reverse transcriptase inhibitors.

5 WARNINGS AND PRECAUTIONS

5.1 Dosing Errors

Phenytoin Sodium Equivalents (PE)

Do not confuse the amount of drug to be given in PE with the concentration of the drug in the vial.

Doses of CEREBYX are always expressed in terms of milligrams of phenytoin sodium equivalents (mg PE). 1 mg PE is equivalent to 1 mg phenytoin sodium.

Do not, therefore, make any adjustment in the recommended doses when substituting CEREBYX for phenytoin sodium or vice versa. For example, if a patient is receiving 1000 mg PE of CEREBYX, that is equivalent to 1000 mg of phenytoin sodium.

Concentration of 50 mg PE/mL

Medication errors associated with CEREBYX have resulted in patients receiving the wrong dose of fosphenytoin. CEREBYX is marketed in 2 mL vials containing a total of 100 mg PE and 10 mL vials containing a total of 500 mg PE. The concentration of each vial is 50 mg PE/mL. Errors have occurred when the concentration of the vial (50 mg PE/mL) was misinterpreted to mean that the total content of the vial was 50 mg PE. These errors have resulted in two- or ten-fold overdoses of CEREBYX since each vial actually contains a total of 100 mg PE or 500 mg PE. In some cases, ten-fold overdoses were associated with fatal outcomes. To help minimize confusion, the prescribed dose of CEREBYX should always be expressed in milligrams of phenytoin equivalents (mg PE) [see Dosage and Administration (2.1)]. Additionally, when ordering and storing CEREBYX, consider displaying the total drug content (i.e., 100 mg PE/ 2 mL or 500 mg PE/ 10 mL) instead of concentration in computer systems, pre-printed orders, and automated dispensing cabinet databases to help ensure that total drug content can be clearly identified. Care should be taken to ensure the appropriate volume of CEREBYX is withdrawn from the vial when preparing the drug for administration. Attention to these details may prevent some CEREBYX medication errors from occurring.

5.2 Cardiovascular Risk Associated with Rapid Infusion

Rapid intravenous administration of CEREBYX increases the risk of adverse cardiovascular reactions, including severe hypotension and cardiac arrhythmias. Cardiac arrhythmias have included bradycardia, heart block, QT interval prolongation, ventricular tachycardia, and ventricular fibrillation which have resulted in asystole, cardiac arrest, and death. Severe complications are most commonly encountered in critically ill patients, elderly patients, and patients with hypotension and severe myocardial insufficiency. However, cardiac events have also been reported in adults and children without underlying cardiac disease or comorbidities and at recommended doses and infusion rates.

The rate of intravenous CEREBYX administration should not exceed 150 mg phenytoin sodium equivalents (PE) per minute in adults and 2 mg PE/kg/min (or 150 mg PE/min, whichever is slower) in pediatric patients [see Dosage and Administration (2.3, 2.4)].

Although the risk of cardiovascular toxicity increases with infusion rates above the recommended infusion rate, these events have also been reported at or below the recommended infusion rate.

As non-emergency therapy, intravenous CEREBYX should be administered more slowly. Because of the risks of cardiac and local toxicity associated with IV CEREBYX, oral phenytoin should be used whenever possible.

Because adverse cardiovascular reactions have occurred during and after infusions, careful cardiac and respiratory monitoring is needed during and after the administration of intravenous CEREBYX. Reduction in rate of administration or discontinuation of dosing may be needed.

5.3 Withdrawal Precipitated Seizure, Status Epilepticus

Antiepileptic drugs should not be abruptly discontinued because of the possibility of increased seizure frequency, including status epilepticus. When, in the judgment of the clinician, the need for dosage reduction, discontinuation, or substitution of alternative antiepileptic medication arises, this should be done gradually. However, in the event of an allergic or hypersensitivity reaction, rapid substitution of alternative therapy may be necessary. In this case, alternative therapy should be an antiepileptic drug not belonging to the hydantoin chemical class.

5.4 Serious Dermatologic Reactions

CEREBYX can cause severe cutaneous adverse reactions (SCARs), which may be fatal. Reported reactions in phenytoin (the active metabolite of CEREBYX)-treated patients have included toxic epidermal necrolysis (TEN), Stevens-Johnson syndrome (SJS), acute generalized exanthematous pustulosis (AGEP), and Drug Reaction with Eosinophilia and Systemic Symptoms (DRESS) [see Warnings and Precautions (5.5)]. The onset of symptoms is usually within 28 days, but can occur later. CEREBYX should be discontinued at the first sign of a rash, unless the rash is clearly not drug-related. If signs or symptoms suggest a severe cutaneous adverse reaction, use of this drug should not be resumed and alternative therapy should be considered. If a rash occurs, the patient should be evaluated for signs and symptoms of SCARs.

Studies in patients of Chinese ancestry have found a strong association between the risk of developing SJS/TEN and the presence of HLA-B*1502, an inherited allelic variant of the HLA B gene, in patients using carbamazepine. Limited evidence suggests that HLA-B*1502 may be a risk factor for the development of SJS/TEN in patients of Asian ancestry taking other antiepileptic drugs associated with SJS/TEN, including phenytoin. In addition, retrospective, case-control, genome-wide association studies in patients of southeast Asian ancestry have also identified an increased risk of SCARs in carriers of the decreased function CYP2C9*3 variant, which has also been associated with decreased clearance of phenytoin. Consider avoiding CEREBYX as an alternative to carbamazepine in patients who are positive for HLA-B*1502 or in CYP2C9*3 carriers.

Should CEREBYX be utilized for CYP2C9*3 carriers, consider starting at the lower end of the dosage range [see Use in Specific Populations (8.7)].

The use of HLA-B*1502 or CYP2C9 genotyping has important limitations and must never substitute for appropriate clinical vigilance and patient management. The role of other possible factors in the development of, and morbidity from, SJS/TEN, such as antiepileptic drug (AED) dose, compliance, concomitant medications, comorbidities, and the level of dermatologic monitoring have not been studied.

5.5 Drug Reaction with Eosinophilia and Systemic Symptoms (DRESS)/Multiorgan Hypersensitivity

Drug Reaction with Eosinophilia and Systemic Symptoms (DRESS), also known as Multiorgan hypersensitivity, has been reported in patients taking antiepileptic drugs, including phenytoin and CEREBYX. Some of these events have been fatal or life-threatening. DRESS typically, although not exclusively, presents with fever, rash, lymphadenopathy, and/or facial swelling, in association with other organ system involvement, such as hepatitis, nephritis, hematological abnormalities, myocarditis, or myositis sometimes resembling an acute viral infection. Eosinophilia is often present. Because this disorder is variable in its expression, other organ systems not noted here may be involved. It is important to note that early manifestations of hypersensitivity, such as fever or lymphadenopathy, may be present even though rash is not evident. If such signs or symptoms are present, the patient should be evaluated immediately. CEREBYX should be discontinued if an alternative etiology for the signs or symptoms cannot be established.

5.6 Hypersensitivity

CEREBYX and other hydantoins are contraindicated in patients who have experienced phenytoin hypersensitivity [see Contraindications (4) and Warnings and Precautions (5.7)]. Additionally, consider alternatives to structurally similar drugs such as carboxamides (e.g., carbamazepine), barbiturates, succinimides, and oxazolidinediones (e.g., trimethadione) in these same patients. Similarly, if there is a history of hypersensitivity reactions to these structurally similar drugs in the patient or immediate family members, consider alternatives to CEREBYX.

5.7 Angioedema

Angioedema has been reported in patients treated with phenytoin and CEREBYX in the postmarketing setting. CEREBYX should be discontinued immediately if symptoms of angioedema, such as facial, perioral, or upper airway swelling occur. CEREBYX should be discontinued permanently if a clear alternative etiology for the reaction cannot be established.

5.8 Hepatic Injury

Cases of acute hepatotoxicity, including infrequent cases of acute hepatic failure, have been reported with phenytoin (the active metabolite of CEREBYX). These events may be part of the spectrum of DRESS or may occur in isolation [see Warnings and Precautions (5.5)]. Other common manifestations include jaundice, hepatomegaly, elevated serum transaminase levels, leukocytosis, and eosinophilia. The clinical course of acute phenytoin hepatotoxicity ranges from prompt recovery to fatal outcomes. In these patients with acute hepatotoxicity, CEREBYX should be immediately discontinued and not re-administered.

5.9 Hematopoietic Complications

Hematopoietic complications, some fatal, have occasionally been reported in association with administration of phenytoin (the active metabolite of CEREBYX). These have included thrombocytopenia, leukopenia, granulocytopenia, agranulocytosis, and pancytopenia with or without bone marrow suppression.

There have been a number of reports that have suggested a relationship between phenytoin and the development of lymphadenopathy (local or generalized), including benign lymph node hyperplasia, pseudolymphoma, lymphoma, and Hodgkin's disease. Although a cause and effect relationship has not been established, the occurrence of lymphadenopathy indicates the need to differentiate such a condition from other types of lymph node pathology. Lymph node involvement may occur with or without symptoms and signs resembling DRESS [see Warnings and Precautions (5.5)].

In all cases of lymphadenopathy, follow-up observation for an extended period is indicated and every effort should be made to achieve seizure control using alternative antiepileptic drugs. Macrocytosis and megaloblastic anemia have occurred, these conditions usually respond to folic acid therapy. Pure red cell aplasia has also been reported with phenytoin.

5.10 Sensory Disturbances

Severe burning, itching, and/or paresthesia were reported by 7 of 16 normal volunteers administered IV CEREBYX at a dose of 1200 mg PE at the maximum rate of administration (150 mg PE/min). The severe sensory disturbance lasted from 3 to 50 minutes in 6 of these subjects and for 14 hours in the seventh subject. In some cases, milder sensory disturbances persisted for as long as 24 hours. The location of the discomfort varied among subjects with the groin mentioned most frequently as an area of discomfort. In a separate cohort of 16 normal volunteers (taken from 2 other studies) who were administered IV CEREBYX at a dose of 1200 mg PE at the maximum rate of administration (150 mg PE/min), none experienced severe disturbances, but most experienced mild to moderate itching or tingling. Patients administered CEREBYX at doses of 20 mg PE/kg at 150 mg PE/min are expected to experience discomfort of some degree. The occurrence and intensity of the discomfort can be lessened by slowing or temporarily stopping the infusion. The effect of continuing infusion unaltered in the presence of these sensations is unknown. No permanent sequelae have been reported thus far. The pharmacologic basis for these positive sensory phenomena is unknown, but other phosphate ester drugs, which deliver smaller phosphate loads, have been associated with burning, itching, and/or tingling predominantly in the groin area.

5.11 Local Toxicity (Including Purple Glove Syndrome)

Edema, discoloration, and pain distal to the site of injection (described as "purple glove syndrome") have also been reported following peripheral intravenous CEREBYX injection. This may or may not be associated with extravasation. The syndrome may not develop for several days after injection.

5.12 Phosphate Load

The phosphate load provided by CEREBYX (0.0037 mmol phosphate/mg PE CEREBYX) should be considered when treating patients who require phosphate restriction, such as those with severe renal impairment.

5.13 Renal or Hepatic Disease or Hypoalbuminemia

Because the fraction of unbound phenytoin (the active metabolite of CEREBYX) is increased in patients with renal or hepatic disease, or in those with hypoalbuminemia, the monitoring of phenytoin serum levels should be based on the unbound fraction in those patients. After IV administration to patients with renal and/or hepatic disease, or in those with hypoalbuminemia, fosphenytoin clearance to phenytoin may be increased without a similar increase in phenytoin clearance. This has the potential to increase the frequency and severity of adverse events.

5.14 Exacerbation of Porphyria

In view of isolated reports associating phenytoin (the active metabolite of CEREBYX) with exacerbation of porphyria, caution should be exercised in using CEREBYX in patients suffering from this disease.

5.15 Teratogenicity and Other Harm to the Newborn

CEREBYX may cause fetal harm when administered to a pregnant woman. Prenatal exposure to phenytoin (the active metabolite of CEREBYX) may increase the risks for congenital malformations and other adverse developmental outcomes [see Use in Specific Populations (8.1)].

Increased frequencies of major malformations (such as orofacial clefts and cardiac defects), and abnormalities characteristic of fetal hydantoin syndrome, including dysmorphic skull and facial features, nail and digit hypoplasia, growth abnormalities (including microcephaly), and cognitive deficits, have been reported among children born to epileptic women who took phenytoin alone or in combination with other antiepileptic drugs during pregnancy. There have been several reported cases of malignancies, including neuroblastoma.

A potentially life-threatening bleeding disorder related to decreased levels of vitamin K-dependent clotting factors may occur in newborns exposed to phenytoin in utero. This drug-induced condition can be prevented with vitamin K administration to the mother before delivery and to the neonate after birth.

5.16 Hyperglycemia

Hyperglycemia, resulting from the inhibitory effect of phenytoin (the active metabolite of CEREBYX) on insulin release, has been reported. Phenytoin may also raise the serum glucose concentrations in diabetic patients.

5.17 Serum Phenytoin Levels above Therapeutic Range

Serum levels of phenytoin (the active metabolite of CEREBYX) sustained above the therapeutic range may produce confusional states referred to as "delirium," "psychosis," or "encephalopathy," or rarely, irreversible cerebellar dysfunction and/or cerebellar atrophy. Accordingly, at the first sign of acute toxicity, serum levels should be immediately checked. CEREBYX dose reduction is indicated if serum levels are excessive; if symptoms persist, administration of CEREBYX should be discontinued.

6 ADVERSE REACTIONS

The following serious adverse reactions are described elsewhere in the labeling:

- Cardiovascular Risk Associated with Rapid Infusion [see Warnings and Precautions (5.2)]
- Withdrawal Precipitated Seizure, Status Epilepticus [see Warnings and Precautions (5.3)]
- Serious Dermatologic Reactions [see Warnings and Precautions (5.4)]
- Drug Reaction with Eosinophilia and Systemic Symptoms (DRESS)/Multiorgan Hypersensitivity [see Warnings and Precautions (5.5)]
- Hypersensitivity [see Warnings and Precautions (5.6)]
- Angioedema [see Warnings and Precautions (5.7)]
- Hepatic Injury [see Warnings and Precautions (5.8)]
- Hematopoietic Complications [see Warnings and Precautions (5.9)]
- Sensory Disturbances [see Warnings and Precautions (5.10)]
- Local Toxicity (Including Purple Glove Syndrome) [see Warnings and Precautions (5.11)]
- Exacerbation of Porphyria [see Warnings and Precautions (5.14)]
- Teratogenicity and Other Harm to the Newborn [see Warnings and Precautions (5.15)]
- Hyperglycemia [see Warnings and Precautions (5.16)]

6.1 Clinical Trials Experience

Because clinical trials are conducted under widely varying conditions, adverse reaction rates observed in the clinical trials of a drug cannot be directly compared to rates in the clinical trials of another drug and may not reflect the rates observed in practice.

The more important adverse clinical reactions caused by the IV use of CEREBYX or phenytoin are cardiovascular collapse and/or CNS depression. Hypotension can occur when either drug is administered rapidly by the IV route. The rate of administration is very important; for CEREBYX, it should not exceed 150 mg PE/min [see Warnings and Precautions (5.2)]. The adverse reactions most commonly observed with the use of CEREBYX in clinical trials were nystagmus, dizziness, pruritus, somnolence, and ataxia. With one exception, these reactions are commonly associated with the administration of IV phenytoin. Pruritus, however, was seen much more often following CEREBYX administration and occurred more often with IV CEREBYX administration than with IM CEREBYX administration. These reactions were dose and rate related; most alert patients (41 of 64; 64%) administered doses of ≥15 mg PE/kg at 150 mg PE/min experienced discomfort of some degree. These sensations, generally described as itching, burning, or tingling, were usually not at the infusion site. The location of the discomfort varied with the groin mentioned most frequently as a site of involvement. The paresthesia and pruritus were transient events that occurred within several minutes of the start of infusion and generally resolved within 10 minutes after completion of CEREBYX infusion. Some patients experienced symptoms for hours. These reactions did not increase in severity with repeated administration. Concurrent adverse events or clinical laboratory change suggesting an allergic process were not seen [see Warnings and Precautions (5.10)]. Approximately 2% of the 859 patients who received CEREBYX in premarketing clinical trials discontinued treatment because of an adverse event. The adverse events most commonly associated with withdrawal were pruritus (0.5%), hypotension (0.3%), and bradycardia (0.2%).

Dose and Rate Dependency of Adverse Reactions Following IV CEREBYX: The incidence of adverse reactions tended to increase as both dose and infusion rate increased. In particular, at doses of ≥15mg PE/kg and rates ≥150 mg PE/min, transient pruritus, tinnitus, nystagmus, somnolence, and ataxia occurred 2 to 3 times more often than at lower doses or rates.

Incidence in Controlled Clinical Trials

All adverse events were recorded during the trials by the clinical investigators using terminology of their own choosing. Similar types of events were grouped into standardized categories using modified COSTART dictionary terminology. These categories are used in the tables and listings below with the frequencies representing the proportion of individuals exposed to CEREBYX or comparative therapy.

Incidence in Controlled Clinical Trials - IV Administration to Adult Patients with Epilepsy or Neurosurgical Patients: Table 4 lists adverse reactions that occurred in at least 2% of patients treated with IV CEREBYX at the maximum dose and rate in a randomized, double-blind, controlled clinical trial where the rates for phenytoin and CEREBYX administration would have resulted in equivalent systemic exposure to phenytoin.

TABLE 4. Adverse Reaction Incidence Following IV Administration at the Maximum Dose and Rate to Adult Patients with Epilepsy or Neurosurgical Patients (Events in at Least 2% of CEREBYX-Treated Patients)
BODY SYSTEM | IV CEREBYX | IV Phenytoin [The study was not designed to assess comparative safety.]
Adverse Event | N=90 | N=22
BODY AS A WHOLE
Pelvic Pain | 4 | 0
Asthenia | 2 | 0
Back Pain | 2 | 0
Headache | 2 | 5
CARDIOVASCULAR
Hypotension | 8 | 9
Vasodilatation | 6 | 5
Tachycardia | 2 | 0
DIGESTIVE
Nausea | 9 | 14
Tongue Disorder | 4 | 0
Dry Mouth | 4 | 5
Vomiting | 2 | 9
NERVOUS
Nystagmus | 44 | 59
Dizziness | 31 | 27
Somnolence | 20 | 27
Ataxia | 11 | 18
Stupor | 8 | 5
Incoordination | 4 | 5
Paresthesia | 4 | 0
Extrapyramidal Syndrome | 4 | 0
Tremor | 3 | 9
Agitation | 3 | 0
Hypesthesia | 2 | 9
Dysarthria | 2 | 0
Vertigo | 2 | 0
Brain Edema | 2 | 5
SKIN AND APPENDAGES
Pruritus | 49 | 5
SPECIAL SENSES
Tinnitus | 9 | 9
Diplopia | 3 | 0
Taste Perversion | 3 | 0
Amblyopia | 2 | 9
Deafness | 2 | 0

Incidence in Clinical Trials - IV Administration to Pediatric Patients with Epilepsy or Neurosurgical Patients: The overall incidence of adverse reactions and the types of adverse reactions seen were similar among children and adults treated with CEREBYX. In an open-label, safety, tolerability, and pharmacokinetic study of fosphenytoin in pediatric subjects (neonates through age 16), the following adverse reactions occurred at a frequency of at least 5% in 96 subjects treated with intravenous CEREBYX: vomiting (21%), nystagmus (18%), ataxia (10%), fever (8%), nervousness (7%), pruritus (6%), somnolence (6%), hypotension (5%), and rash (5%).

Incidence in Controlled Trials - IM Administration to Adult Patients with Epilepsy: Table 5 lists adverse reactions that occurred in at least 2% of CEREBYX-treated patients in a double-blind, randomized, controlled clinical trial of adult epilepsy patients receiving either IM CEREBYX substituted for oral phenytoin or continuing oral phenytoin. Both treatments were administered for 5 days.

TABLE 5. Adverse Reaction Incidence Following Substitution of IM CEREBYX for Oral Phenytoin in Adult Patients with Epilepsy (Events in at Least 2% of CEREBYX-Treated Patients)
BODY SYSTEM | IM CEREBYX | Oral Phenytoin [The study was not designed to assess comparative safety.]
Adverse Event | N=179 | N=61
BODY AS A WHOLE
Headache | 9 | 5
Asthenia | 9 | 3
DIGESTIVE
Nausea | 5 | 0
Vomiting | 3 | 0
HEMATOLOGIC AND LYMPHATIC
Ecchymosis | 7 | 5
NERVOUS
Nystagmus | 15 | 8
Tremor | 10 | 13
Ataxia | 8 | 8
Incoordination | 8 | 5
Somnolence | 7 | 10
Dizziness | 5 | 3
Paresthesia | 4 | 3
Reflexes Decreased | 3 | 5
SKIN AND APPENDAGES
Pruritus | 3 | 0

Adverse Events During Clinical Trials in Adult and Pediatric Patients

CEREBYX has been administered to approximately 900 individuals during clinical trials. Adverse events seen at least twice are listed in the following, except those already included in previous tables and listings. Events are further classified within body system categories and enumerated in order of decreasing frequency using the following definitions: frequent adverse events are defined as those occurring in greater than 1/100 individuals; infrequent adverse events are those occurring in 1/100 to 1/1000 individuals.

Body as a Whole: Frequent: fever, injection-site reaction, infection, chills, face edema, injection-site pain; Infrequent: sepsis, injection-site inflammation, injection-site edema, injection-site hemorrhage, flu syndrome, malaise, generalized edema, shock, photosensitivity reaction, cachexia, cryptococcosis.

Cardiovascular: Frequent: hypertension; Infrequent: cardiac arrest, migraine, syncope, cerebral hemorrhage, palpitation, sinus bradycardia, atrial flutter, bundle branch block, cardiomegaly, cerebral infarct, postural hypotension, pulmonary embolus, QT interval prolongation, thrombophlebitis, ventricular extrasystoles, congestive heart failure.

Digestive: Frequent: constipation; Infrequent: dyspepsia, diarrhea, anorexia, gastrointestinal hemorrhage, increased salivation, liver function tests abnormal, tenesmus, tongue edema, dysphagia, flatulence, gastritis, ileus.

Endocrine: Infrequent: diabetes insipidus.

Hematologic and Lymphatic: Infrequent: thrombocytopenia, anemia, leukocytosis, cyanosis, hypochromic anemia, leukopenia, lymphadenopathy, petechia [see Warnings and Precautions (5.9)].

Laboratory Test Abnormality: Phenytoin (the active metabolite of CEREBYX) may cause increased serum levels of glucose and alkaline phosphatase.

Metabolic and Nutritional: Frequent: hypokalemia; Infrequent: hyperglycemia, hypophosphatemia, alkalosis, acidosis, dehydration, hyperkalemia, ketosis.

Musculoskeletal: Frequent: myasthenia; Infrequent: myopathy, leg cramps, arthralgia, myalgia.

Nervous: Frequent: reflexes increased, speech disorder, dysarthria, intracranial hypertension, thinking abnormal, nervousness; Infrequent: confusion, twitching, Babinski sign positive, circumoral paresthesia, hemiplegia, hypotonia, convulsion, extrapyramidal syndrome, insomnia, meningitis, depersonalization, CNS depression, depression, hypokinesia, hyperkinesia, paralysis, psychosis, aphasia, emotional lability, coma, hyperesthesia, myoclonus, personality disorder, acute brain syndrome, encephalitis, subdural hematoma, encephalopathy, hostility, akathisia, amnesia, neurosis.

Respiratory: Frequent: pneumonia; Infrequent: pharyngitis, sinusitis, hyperventilation, rhinitis, apnea, aspiration pneumonia, asthma, dyspnea, atelectasis, cough increased, sputum increased, epistaxis, hypoxia, pneumothorax, hemoptysis, bronchitis.

Skin and Appendages: Frequent: rash; Infrequent: maculopapular rash, urticaria, sweating, skin discoloration, contact dermatitis, pustular rash, skin nodule.

Special Senses: Infrequent: visual field defect, eye pain, conjunctivitis, photophobia, hyperacusis, mydriasis, parosmia, ear pain, taste loss.

Urogenital: Infrequent: urinary retention, oliguria, dysuria, vaginitis, albuminuria, genital edema, kidney failure, polyuria, urethral pain, urinary incontinence, vaginal moniliasis.

6.2 Postmarketing Experience

The following adverse reactions have been identified during post-approval use of phenytoin or fosphenytoin. Because these reactions are reported voluntarily from a population of uncertain size, it is not always possible to reliably estimate their frequency or establish a causal relationship to drug exposure.

Body as a Whole: Anaphylaxis, angioedema [see Warnings and Precautions (5.7)]

Hematologic: Pure red cell aplasia [see Warnings and Precautions (5.9)]

Laboratory Test Abnormality: Phenytoin or CEREBYX may decrease serum concentrations of T4. It may also produce lower than normal values for dexamethasone or metyrapone tests. Phenytoin may also cause increased serum levels of gamma glutamyl transpeptidase (GGT).

Nervous System Disorders: Dyskinesia

7 DRUG INTERACTIONS

Fosphenytoin is extensively bound to human plasma proteins. Drugs highly bound to albumin could increase the unbound fraction of fosphenytoin. Although, it is unknown whether this could result in clinically significant effects, caution is advised when administering CEREBYX with other drugs that significantly bind to serum albumin. The most significant drug interactions following administration of CEREBYX are expected to occur with drugs that interact with phenytoin. Phenytoin is extensively bound to serum plasma proteins and is prone to competitive displacement. Phenytoin is primarily metabolized by the hepatic cytochrome P450 enzyme CYP2C9 and to a lesser extent by CYP2C19 and is particularly susceptible to inhibitory drug interactions because it is subject to saturable metabolism. Inhibition of metabolism may produce significant increases in circulating phenytoin concentrations and enhance the risk of drug toxicity. Monitoring of phenytoin serum levels is recommended when a drug interaction is suspected.

Phenytoin or CEREBYX is a potent inducer of hepatic drug-metabolizing enzymes.

7.1 Drugs that Affect Phenytoin or CEREBYX

Table 6 includes commonly occurring drug interactions that affect phenytoin (the active metabolite of CEREBYX) concentrations. However, this list is not intended to be inclusive or comprehensive. Individual prescribing information from relevant drugs should be consulted.

The addition or withdrawal of these agents in patients on phenytoin therapy may require an adjustment of the phenytoin dose to achieve optimal clinical outcome.

Table 6. Drugs That Affect Phenytoin Concentrations
Interacting Agent | Examples
Drugs that may increase phenytoin serum levels
Antiepileptic drugs | Ethosuximide, felbamate, oxcarbazepine, methsuximide, topiramate
Azoles | Fluconazole, ketoconazole, itraconazole, miconazole, voriconazole
Antineoplastic agents | Capecitabine, fluorouracil
Antidepressants | Fluoxetine, fluvoxamine, sertraline
Gastric acid reducing agents | H2 antagonists (cimetidine), omeprazole
Sulfonamides | Sulfamethizole, sulfaphenazole, sulfadiazine, sulfamethoxazole-trimethoprim
Other | Acute alcohol intake, amiodarone, chloramphenicol, chlordiazepoxide, disulfiram, estrogen, fluvastatin, isoniazid, methylphenidate, phenothiazines, salicylates, ticlopidine, tolbutamide, trazodone, warfarin
Drugs that may decrease phenytoin serum levels
Antineoplastic agents usually in combination | Bleomycin, carboplatin, cisplatin, doxorubicin, methotrexate
Antiviral agents | Fosamprenavir, nelfinavir, ritonavir
Antiepileptic drugs | Carbamazepine, vigabatrin
Other | Chronic alcohol abuse, diazepam, diazoxide, folic acid, reserpine, rifampin, St. John's wort, [The induction potency of St. John's wort may vary widely based on preparation.] theophylline
Drugs that may either increase or decrease phenytoin serum levels
Antiepileptic drugs | Phenobarbital, valproate sodium, valproic acid

7.2 Drugs Affected by Phenytoin or CEREBYX

Table 7 includes commonly occurring drug interactions affected by phenytoin (the active metabolite of CEREBYX). However, this list is not intended to be inclusive or comprehensive. Individual drug package inserts should be consulted. The addition or withdrawal of phenytoin during concomitant therapy with these agents may require adjustment of the dose of these agents to achieve optimal clinical outcome.

Table 7: Drugs Affected by Phenytoin
Interacting Agent | Examples
Drugs whose efficacy is impaired by phenytoin
Azoles | Fluconazole, ketoconazole, itraconazole, posaconazole, voriconazole
Antineoplastic agents | Irinotecan, paclitaxel, teniposide
Delavirdine | Phenytoin can substantially reduce the concentrations of delavirdine. This can lead to loss of virologic response and possible resistance [see Contraindications (4)].
Neuromuscular blocking agents | Cisatracurium, pancuronium, rocuronium and vecuronium: resistance to the neuromuscular blocking action of the nondepolarizing neuromuscular blocking agents has occurred in patients chronically administered phenytoin. Whether or not phenytoin has the same effect on other non-depolarizing agents is unknown.; Prevention or Management: Patients should be monitored closely for more rapid recovery from neuromuscular blockade than expected, and infusion rate requirements may be higher.
Warfarin | Increased and decreased PT/INR responses have been reported when phenytoin is coadministered with warfarin.
Other | Corticosteroids, doxycycline, estrogens, furosemide, oral contraceptives, paroxetine, quinidine, rifampin, sertraline, theophylline, and vitamin D
Drugs whose level is decreased by phenytoin
Anticoagulants | Apixaban, dabigatran, edoxaban, rivaroxaban
Antiepileptic drugs [The effect of phenytoin on phenobarbital, valproic acid and sodium valproate serum levels is unpredictable.] | Carbamazepine, felbamate, lamotrigine, topiramate, oxcarbazepine, lacosamide
Antiplatelets | Ticagrelor
Antilipidemic agents | Atorvastatin, fluvastatin, simvastatin
Antiviral agents | Efavirenz, lopinavir/ritonavir, indinavir, nelfinavir, ritonavir, saquinavir Fosamprenavir: phenytoin when given with fosamprenavir alone may decrease the concentration of amprenavir, the active metabolite. Phenytoin when given with the combination of fosamprenavir and ritonavir may increase the concentration of amprenavir
Calcium channel blockers | Nifedipine, nimodipine, nisoldipine, verapamil
Other | Albendazole (decreases active metabolite), chlorpropamide, clozapine, cyclosporine, digoxin, disopyramide, folic acid, methadone, mexiletine, praziquantel, quetiapine

7.3 Hyperammonemia with Concomitant Use of Valproate

Concomitant administration of phenytoin and valproate has been associated with an increased risk of valproate-associated hyperammonemia. Patients treated concomitantly with these two drugs should be monitored for signs and symptoms of hyperammonemia.

7.4 Drug/Laboratory Test Interactions

Care should be taken when using immunoanalytical methods to measure serum phenytoin concentrations following CEREBYX administration.

8 USE IN SPECIFIC POPULATIONS

8.1 Pregnancy

Pregnancy Exposure Registry

There is a pregnancy exposure registry that monitors pregnancy outcomes in women exposed to antiepileptic drugs (AEDs), such as CEREBYX, during pregnancy. Physicians are advised to recommend that pregnant patients taking CEREBYX enroll in the North American Antiepileptic Drug (NAAED) Pregnancy Registry. This can be done by calling the toll-free number 1-888-233-2334, and must be done by patients themselves. Information on the registry can also be found at the website http://www.aedpregnancyregistry.org/.

Risk Summary

In humans, prenatal exposure to phenytoin (the active metabolite of CEREBYX) may increase the risks for congenital malformations and other adverse developmental outcomes. Prenatal phenytoin exposure is associated with an increased incidence of major malformations, including orofacial clefts and cardiac defects. In addition, the fetal hydantoin syndrome, a pattern of abnormalities including dysmorphic skull and facial features, nail and digit hypoplasia, growth abnormalities (including microcephaly), and cognitive deficits has been reported among children born to epileptic women who took phenytoin alone or in combination with other antiepileptic drugs during pregnancy [see Data]. There have been several reported cases of malignancies, including neuroblastoma, in children whose mothers received phenytoin during pregnancy.

Administration of phenytoin to pregnant animals resulted in an increased incidence of fetal malformations and other manifestations of developmental toxicity (including embryofetal death, growth impairment, and behavioral abnormalities) in multiple species at clinically relevant doses [see Data].

In the U.S. general population, the estimated background risk of major birth defects and of miscarriage in clinically recognized pregnancies is 2 to 4% and 15 to 20%, respectively. The background risk of major birth defects and miscarriage for the indicated population is unknown.

Clinical Considerations

Disease-associated maternal risk

An increase in seizure frequency may occur during pregnancy because of altered phenytoin pharmacokinetics. Periodic measurement of serum phenytoin concentrations may be valuable in the management of pregnant women as a guide to appropriate adjustment of dosage [see Dosage and Administration (2.5, 2.9)]. However, postpartum restoration of the original dosage will probably be indicated.

Fetal/Neonatal adverse reactions

A potentially life-threatening bleeding disorder related to decreased levels of vitamin K-dependent clotting factors may occur in newborns exposed to phenytoin in utero. This drug-induced condition can be prevented with vitamin K administration to the mother before delivery and to the neonate after birth.

Data

Human Data

Meta-analyses using data from published observational studies and registries have estimated an approximately 2.4-fold increased risk for any major malformation in children with prenatal phenytoin exposure compared to controls. An increased risk of heart defects, facial clefts, and digital hypoplasia has been reported. The fetal hydantoin syndrome is a pattern of congenital anomalies including craniofacial anomalies, nail and digital hypoplasia, prenatal-onset growth deficiency, and neurodevelopmental deficiencies.

Animal Data

Administration of phenytoin to pregnant rats, rabbits, and mice during organogenesis resulted in embryofetal death, fetal malformations, and decreased fetal growth. Malformations (including craniofacial, cardiovascular, neural, limb, and digit abnormalities) were observed in rats, rabbits, and mice at doses as low as 100, 75, and 12.5 mg/kg, respectively.

8.2 Lactation

Risk Summary

It is not known whether fosphenytoin is secreted in human milk. Following administration of phenytoin (the active metabolite of CEREBYX), phenytoin is secreted in human milk. The developmental and health benefits of breastfeeding should be considered along with the mother's clinical need for CEREBYX and any potential adverse effects on the breastfed infant from CEREBYX or from the underlying maternal condition.

8.4 Pediatric Use

CEREBYX is indicated for the treatment of generalized tonic-clonic status epilepticus and prevention and treatment of seizures occurring during neurosurgery in all pediatric age groups [see Indications and Usage (1) and Dosage and Administration (2.3, 2.4)]. Because rapid intravenous administration of CEREBYX increases the risk of adverse cardiovascular reactions, the rate of administration should not exceed 2 mg PE/kg/min (or 150 mg PE/min, whichever is slower) in pediatric patients [see Dosage and Administration (2.3, 2.4) and Warnings and Precautions (5.2)].

8.5 Geriatric Use

No systematic studies in geriatric patients have been conducted. Phenytoin clearance tends to decrease with increasing age [see Clinical Pharmacology (12.3)]. Lower or less frequent dosing may be required [see Clinical Pharmacology (12.3) and Dosage and Administration (2.8)].

8.6 Renal and/or Hepatic Impairment, or Hypoalbuminemia

The liver is the site of biotransformation. Patients with impaired liver function, elderly patients, or those who are gravely ill may show early toxicity.

Because the fraction of unbound phenytoin (the active metabolite of CEREBYX) is increased in patients with renal or hepatic disease, or in those with hypoalbuminemia, the monitoring of phenytoin serum levels should be based on the unbound fraction in those patients.

After IV administration to patients with renal and/or hepatic disease, or in those with hypoalbuminemia, fosphenytoin clearance to phenytoin may be increased without a similar increase in phenytoin clearance. This has the potential to increase the frequency and severity of adverse events.

8.7 Use in Patients with Decreased CYP2C9 Function

Patients who are intermediate or poor metabolizers of CYP2C9 substrates (e.g., *1/*3, *2/*2, *3/*3) may exhibit increased phenytoin serum concentrations compared to patients who are normal metabolizers (e.g., *1/*1). Thus, patients who are known to be intermediate or poor metabolizers may ultimately require lower doses to maintain similar steady-state concentrations compared to normal metabolizers. In patients who are known to be carriers of the decreased function CYP2C9*2 or *3 alleles (intermediate and poor metabolizers), consider starting at the low end of the dosage range and monitor serum concentrations to maintain total phenytoin concentrations of 10 to 20 mcg/mL. If early signs of dose-related central nervous system (CNS) toxicity develop, serum concentrations should be checked immediately [see Clinical Pharmacology (12.5)].

10 OVERDOSAGE

Nausea, vomiting, lethargy, tachycardia, bradycardia, asystole, cardiac arrest, hypotension, syncope, hypocalcemia, metabolic acidosis, and death have been reported in cases of overdosage with CEREBYX.

Because CEREBYX is a prodrug of phenytoin, the following information about phenytoin overdosage may be helpful. Initial symptoms of acute phenytoin toxicity are nystagmus, ataxia, and dysarthria. Other signs include tremor, hyperreflexia, lethargy, slurred speech, nausea, vomiting, coma, and hypotension. Death is caused by respiratory and circulatory depression. The lethal dose of phenytoin in adults is estimated to be 2 to 5 grams. The lethal dose in pediatrics is not known.

There are marked variations among individuals with respect to serum phenytoin concentrations where toxicity occurs. Lateral gaze nystagmus usually appears at 20 µg/mL, ataxia at 30 µg/mL, and dysarthria and lethargy appear when the serum concentration is over 40 µg/mL. However, phenytoin concentrations as high as 50 µg/mL have been reported without evidence of toxicity. As much as 25 times the therapeutic phenytoin dose has been taken, resulting in serum phenytoin concentrations over 100 µg/mL, with complete recovery. Irreversible cerebellar dysfunction and atrophy have been reported after overdosage.

Formate and phosphate are metabolites of CEREBYX and therefore may contribute to signs of toxicity following overdosage. Signs of formate toxicity are similar to those of methanol toxicity and are associated with severe anion-gap metabolic acidosis. Large amounts of phosphate, delivered rapidly, could potentially cause hypocalcemia with paresthesia, muscle spasms, and seizures. Ionized free calcium levels can be measured and, if low, used to guide treatment.

Treatment: Treatment is nonspecific since there is no known antidote to CEREBYX or phenytoin overdosage.

The adequacy of the respiratory and circulatory systems should be carefully observed, and appropriate supportive measures employed. Hemodialysis can be considered since phenytoin (the active metabolite of CEREBYX) is not completely bound to plasma proteins. Total exchange transfusion has been used in the treatment of severe intoxication in children.

In acute overdosage the possibility of other CNS depressants, including alcohol, should be borne in mind.

11 DESCRIPTION

CEREBYX® (fosphenytoin sodium injection) is a prodrug intended for parenteral administration; its active metabolite is phenytoin. 1.5 mg of fosphenytoin sodium is equivalent to 1 mg phenytoin sodium, and is referred to as 1 mg phenytoin sodium equivalents (PE). The amount and concentration of fosphenytoin is always expressed in terms of mg PE.

The pharmacological class of the fosphenytoin sodium is hydantoin derivative, and the therapeutic class is anticonvulsant.

CEREBYX is marketed in 2 mL vials containing a total of 100 mg PE/2 mL (50 mg PE/mL) and 10 mL vials containing a total of 500 mg PE/10 mL (50 mg PE/mL), for intravenous or intramuscular administration. The concentration of each vial is 50 mg PE/mL. CEREBYX is supplied in vials as a sterile solution in Water for Injection, USP, and Tromethamine, USP (TRIS) (12.11 mg/mL), buffer adjusted to pH 8.6 to 9.0 with either Hydrochloric Acid, NF, or Sodium Hydroxide, NF. CEREBYX is a clear, colorless to pale yellow, sterile solution.

The chemical name of fosphenytoin is 5,5-diphenyl-3-[(phosphonooxy)methyl]-2,4-imidazolidinedione disodium salt. The molecular structure of fosphenytoin is:

The molecular weight of fosphenytoin is 406.24.

12 CLINICAL PHARMACOLOGY

12.1 Mechanism of Action

Fosphenytoin is a prodrug of phenytoin and accordingly, its anticonvulsant effects are attributable to phenytoin. The precise mechanism by which phenytoin exerts its therapeutic effect has not been established but is thought to involve the voltage-dependent blockade of membrane sodium channels resulting in a reduction in sustained high-frequency neuronal discharges.

12.3 Pharmacokinetics

Fosphenytoin

Absorption

Intravenous: When CEREBYX is administered by IV infusion, maximum plasma fosphenytoin concentrations are achieved at the end of the infusion.

Intramuscular: Fosphenytoin is completely bioavailable following IM administration of CEREBYX. Peak concentrations occur at approximately 30 minutes postdose. Plasma fosphenytoin concentrations following IM administration are lower but more sustained than those following IV administration due to the time required for absorption of fosphenytoin from the injection site.

Distribution

Fosphenytoin is extensively bound (95% to 99%) to human plasma proteins, primarily albumin. Binding to plasma proteins is saturable with the result that the percent bound decreases as total fosphenytoin concentrations increase. Fosphenytoin displaces phenytoin from protein binding sites. The volume of distribution of fosphenytoin increases with CEREBYX dose and rate, and ranges from 4.3 to 10.8 liters.

Elimination

The conversion half-life of fosphenytoin to phenytoin is approximately 15 minutes.

Metabolism

Following parenteral administration of CEREBYX, fosphenytoin is converted to the anticonvulsant phenytoin. The mechanism of fosphenytoin conversion has not been determined, but phosphatases probably play a major role. Fosphenytoin is metabolized to phenytoin, phosphate, and formate. For every mmol of fosphenytoin administered, one mmol of phenytoin is produced. The hydrolysis of fosphenytoin to phenytoin yields two metabolites, phosphate and formaldehyde. Formaldehyde is subsequently converted to formate, which is in turn metabolized via a folate dependent mechanism. Although phosphate and formaldehyde (formate) have potentially important biological effects, these effects typically occur at concentrations considerably in excess of those obtained when CEREBYX is administered under conditions of use recommended in this labeling.

Excretion

Fosphenytoin is not excreted in urine.

Phenytoin (after CEREBYX administration)

In general, IM administration of CEREBYX generates systemic phenytoin concentrations that are similar enough to oral phenytoin sodium to allow essentially interchangeable use. The pharmacokinetics of fosphenytoin following IV administration of CEREBYX, however, are complex, and when used in an emergency setting (e.g., status epilepticus), differences in rate of availability of phenytoin could be critical. Studies have therefore empirically determined an infusion rate for CEREBYX that gives a rate and extent of phenytoin systemic availability similar to that of a 50 mg/min phenytoin sodium infusion. A dose of 15 to 20 mg PE/kg of CEREBYX infused at 100 to 150 mg PE/min yields plasma free phenytoin concentrations over time that approximate those achieved when an equivalent dose of phenytoin sodium (e.g., parenteral DILANTIN®) is administered at 50 mg/min [see Dosage and Administration (2.3) and Warnings and Precautions (5.2)].

FIGURE 1. | Mean plasma unbound phenytoin concentrations following IV administration of 1200 mg PE CEREBYX infused at 100 mg PE/min (triangles) or 150 mg PE/min (squares) and 1200 mg Dilantin infused at 50 mg/min (diamonds) to healthy subjects (N = 12). Inset shows time course for the entire 96-hour sampling period.

Following administration of single IV CEREBYX doses of 400 to 1200 mg PE, mean maximum total phenytoin concentrations increase in proportion to dose, but do not change appreciably with changes in infusion rate. In contrast, mean maximum unbound phenytoin concentrations increase with both dose and rate.

Absorption:

Fosphenytoin is completely converted to phenytoin following IV administration, with a half-life of approximately 15 minutes. Fosphenytoin is also completely converted to phenytoin following IM administration and plasma total phenytoin concentrations peak in approximately 3 hours.

Distribution:

Phenytoin is highly bound to plasma proteins, primarily albumin, although to a lesser extent than fosphenytoin. In the absence of fosphenytoin, approximately 12% of total plasma phenytoin is unbound over the clinically relevant concentration range. However, fosphenytoin displaces phenytoin from plasma protein binding sites. This increases the fraction of phenytoin unbound (up to 30% unbound) during the period required for conversion of fosphenytoin to phenytoin (approximately 0.5 to 1 hour postinfusion).

Elimination:

Mean total phenytoin half-life values (12.0 to 28.9 hr) following CEREBYX administration at these doses are similar to those after equal doses of parenteral Dilantin and tend to be greater at higher plasma phenytoin concentrations.

Metabolism

Phenytoin derived from administration of CEREBYX is extensively metabolized in the liver by the cytochrome P450 enzyme CYP2C9 and to a lesser extent by CYP2C19. Phenytoin hepatic metabolism is saturable, and following administration of single IV CEREBYX doses of 400 to 1200 mg PE, total and unbound phenytoin AUC values increase disproportionately with dose.

Excretion

Phenytoin derived from administration of CEREBYX is excreted in urine primarily as 5-(p-hydroxyphenyl)-5-phenylhydantoin and its glucuronide; little unchanged phenytoin (1% to 5% of the CEREBYX dose) is recovered in urine.

Specific Populations

Age: Geriatric Population:

The effect of age on the pharmacokinetics of fosphenytoin was evaluated in patients 5 to 98 years of age. Patient age had no significant impact on fosphenytoin pharmacokinetics. Phenytoin clearance tends to decrease with increasing age (20% less in patients over 70 years of age relative to that in patients 20 to 30 years of age).

Sex/Race:

Gender and race have no significant impact on fosphenytoin or phenytoin pharmacokinetics.

Renal or Hepatic Impairment:

Increased fraction of unbound phenytoin (the active metabolite of CEREBYX) in patients with renal or hepatic disease, or in those with hypoalbuminemia has been reported.

Pregnancy:

It has been reported in the literature that the plasma clearance of phenytoin (the active metabolite of CEREBYX) generally increased during pregnancy, reached a peak in the third trimester and returned to the level of pre-pregnancy after few weeks or months of delivery [see Dosage and Administration (2.9)].

Drug Interaction Studies

Phenytoin derived from administration of CEREBYX is extensively metabolized in the liver by the cytochrome P450 enzyme CYP2C9 and to a lesser extent by CYP2C19 [see Drug Interactions (7.1, 7.2)]. No drugs are known to interfere with the conversion of fosphenytoin to phenytoin. Conversion could be affected by alterations in the level of phosphatase activity, but given the abundance and wide distribution of phosphatases in the body it is unlikely that drugs would affect this activity enough to affect conversion of fosphenytoin to phenytoin.

The pharmacokinetics and protein binding of fosphenytoin, phenytoin, and diazepam were not altered when diazepam and CEREBYX were concurrently administered in single submaximal doses.

12.5 Pharmacogenomics

CYP2C9 activity is decreased in individuals with genetic variants such as the CYP2C9*2 and CYP2C9*3 alleles. Carriers of variant alleles, resulting in intermediate (e.g., *1/*3, *2/*2) or poor metabolism (e.g., *2/*3, *3/*3) have decreased clearance of phenytoin. Other decreased or nonfunctional CYP2C9 alleles may also result in decreased clearance of phenytoin (e.g., *5, *6, *8, *11).

The prevalence of the CYP2C9 poor metabolizer phenotype is approximately 2–3% in the White population, 0.5–4% in the Asian population, and <1% in the African American population. The CYP2C9 intermediate phenotype prevalence is approximately 35% in the White population, 24% in the African American population, and 15–36% in the Asian population [see Warnings and Precautions (5.4) and Use in Specific Populations (8.7)].

13 NONCLINICAL TOXICOLOGY

13.1 Carcinogenesis, Mutagenesis, Impairment of Fertility

Carcinogenesis [see Warnings and Precautions (5.9)]

The carcinogenic potential of fosphenytoin has not been assessed. In carcinogenicity studies, phenytoin (active metabolite of fosphenytoin) was administered in the diet to mice (10, 25, or 45 mg/kg/day) and rats (25, 50, or 100 mg/kg/day) for 2 years. The incidences of hepatocellular tumors were increased in male and female mice at the highest dose. No increases in tumor incidence were observed in rats. The highest doses tested in these studies were associated with peak plasma phenytoin levels below human therapeutic concentrations.

In carcinogenicity studies reported in the literature, phenytoin was administered in the diet for 2 years at doses up to 600 ppm (approximately 160 mg/kg/day) to mice and up to 2400 ppm (approximately 120 mg/kg/day) to rats. The incidences of hepatocellular tumors were increased in female mice at all but the lowest dose tested. No increases in tumor incidence were observed in rats.

Mutagenesis

An increase in structural chromosome aberrations were observed in cultured V79 Chinese hamster lung cells exposed to fosphenytoin in the presence of metabolic activation. No evidence of mutagenicity was observed in bacteria (Ames test) or Chinese hamster lung cells in vitro, and no evidence for clastogenic activity was observed in an in vivo mouse bone marrow micronucleus assay.

Impairment of Fertility

Fosphenytoin was administered to male and female rats during mating and continuing in females throughout gestation and lactation at doses of 50 mg PE/kg or higher. No effects on fertility were observed in males. In females, altered estrous cycles, delayed mating, prolonged gestation length, and developmental toxicity were observed at all doses, which were associated with maternal toxicity. The lowest dose tested is approximately 40% of the maximum human loading dose on a mg/m^2 basis.

14 CLINICAL STUDIES

Infusion tolerance was evaluated in clinical studies. One double-blind study assessed infusion-site tolerance of equivalent loading doses (15 to 20 mg PE/kg) of CEREBYX infused at 150 mg PE/min or phenytoin infused at 50 mg/min. The study demonstrated better local tolerance (pain and burning at the infusion site), fewer disruptions of the infusion, and a shorter infusion period for CEREBYX-treated patients (Table 8).

TABLE 8. Infusion Tolerance of Equivalent Loading Doses of IV CEREBYX and IV Phenytoin
 | IV CEREBYX N=90 | IV Phenytoin N=22
Local Intolerance | 9% [Percent of patients] | 90%
Infusion Disrupted | 21% | 67%
Average Infusion Time | 13 min | 44 min

CEREBYX-treated patients, however, experienced more systemic sensory disturbances [see Warnings and Precautions (5.10)]. Infusion disruptions in CEREBYX-treated patients were primarily due to systemic burning, pruritus, and/or paresthesia while those in phenytoin-treated patients were primarily due to pain and burning at the infusion site (see Table 8). In a double-blind study investigating temporary substitution of CEREBYX for oral phenytoin, IM CEREBYX was as well-tolerated as IM placebo. IM CEREBYX resulted in a slight increase in transient, mild to moderate local itching (23% of CEREBYX-treated patients vs 11% of IM placebo-treated patients at any time during the study). This study also demonstrated that equimolar doses of IM CEREBYX may be substituted for oral phenytoin sodium with no dosage adjustments needed when initiating IM or returning to oral therapy. In contrast, switching between IM and oral phenytoin requires dosage adjustments because of slow and erratic phenytoin absorption from muscle.

16 HOW SUPPLIED/STORAGE AND HANDLING

16.1 How Supplied

CEREBYX Injection is a clear, colorless to pale yellow solution supplied as follows:

mg phenytoin sodium equivalents (PE) per vial | Volume per vial (mL) | Package Configuration | NDC
500 mg PE/10 mL vial | 10 mL per vial | Package contains 10 vials of NDC 0069-6001-10 | NDC 0069-6001-21
100 mg PE/2 mL vial | 2 mL per vial | Package contains 25 vials of NDC 0069-6001-02 | NDC 0069-6001-25

Both sizes of vials contain Tromethamine, USP (TRIS), Hydrochloric Acid, NF, or Sodium Hydroxide, NF, and Water for Injection, USP.

CEREBYX should always be prescribed in phenytoin sodium equivalents (PE) [see Dosage and Administration (2.1) and Warnings and Precautions (5.1)].

1.5 mg of fosphenytoin sodium is equivalent to 1 mg phenytoin sodium, and is referred to as 1 mg PE. The amount and concentration of fosphenytoin is always expressed in terms of mg of phenytoin sodium equivalents (PE). Fosphenytoin's weight is expressed as phenytoin sodium equivalents to avoid the need to perform molecular weight-based adjustments when substituting fosphenytoin for phenytoin or vice versa.

16.2 Storage and Handling

Store under refrigeration at 2°C to 8°C (36°F to 46°F). The product should not be stored at room temperature for more than 48 hours. Vials that develop particulate matter should not be used.

Injection vials are single-dose only. After opening, any unused product should be discarded.

17 PATIENT COUNSELING INFORMATION

Cardiovascular Risk Associated with Rapid Infusion

Inform patients that rapid intravenous administration of CEREBYX increases the risk of adverse cardiovascular reactions, including severe hypotension and cardiac arrhythmias. Cardiac arrhythmias have included bradycardia, heart block, ventricular tachycardia, and ventricular fibrillation which have resulted in asystole, cardiac arrest, and death. Patients should report cardiac signs or symptoms to their healthcare provider [see Warnings and Precautions (5.2)].

Withdrawal of Antiepileptic Drugs

Advise patients not to discontinue use of CEREBYX without consulting with their healthcare provider. CEREBYX should normally be gradually withdrawn to reduce the potential for increased seizure frequency and status epilepticus [see Warnings and Precautions (5.3)].

Serious Dermatologic Reactions

Advise patients of the early signs and symptoms of severe cutaneous adverse reactions and to report any occurrence immediately to a physician [see Warnings and Precautions (5.4)].

Potential Signs of Drug Reaction with Eosinophilia and Systemic Symptoms (DRESS) and Other Systemic Reactions

Advise patients of the early toxic signs and symptoms of potential hematologic, dermatologic, hypersensitivity, or hepatic reactions. These symptoms may include, but are not limited to, fever, sore throat, rash, ulcers in the mouth, easy bruising, lymphadenopathy, facial swelling, and petechial or purpuric hemorrhage, and in the case of liver reactions, anorexia, nausea/vomiting, or jaundice. Advise the patient that, because these signs and symptoms may signal a serious reaction, that they must report any occurrence immediately to a physician. In addition, advise the patient that these signs and symptoms should be reported even if mild or when occurring after extended use [see Warnings and Precautions (5.4, 5.5, 5.6, 5.8, 5.9)].

Angioedema

Advise patients to discontinue CEREBYX and seek immediate medical care if they develop signs or symptoms of angioedema such as facial, perioral, or upper airway swelling [see Warnings and Precautions (5.7)].

Hyperglycemia

Advise patients that CEREBYX may cause an increase in blood glucose levels [see Warnings and Precautions (5.16)].

Effects of Alcohol Use and Other Drugs and Over-the-Counter Drug Interactions

Caution patients against the use of other drugs or alcoholic beverages without first seeking their physician's advice [see Drug Interactions (7.1, 7.2)].

Inform patients that certain over-the-counter medications (e.g., cimetidine and omeprazole), vitamins (e.g., folic acid), and herbal supplements (e.g., St. John's wort) can alter their phenytoin levels.

Use in Pregnancy

Inform pregnant women and women of childbearing potential that use of CEREBYX during pregnancy can cause fetal harm, including an increased risk for cleft lip and/or cleft palate (oral clefts), cardiac defects, dysmorphic skull and facial features, nail and digit hypoplasia, growth abnormalities (including microcephaly), and cognitive deficits. When appropriate, counsel pregnant women and women of childbearing potential about alternative therapeutic options. Advise women of childbearing potential who are not planning a pregnancy to use effective contraception while using CEREBYX, keeping in mind that there is a potential for decreased hormonal contraceptive efficacy [see Drug Interactions (7.2)].

Instruct patients to notify their physician if they become pregnant or intend to become pregnant during therapy, and to notify their physician if they are breastfeeding or intend to breastfeed during therapy [see Use in Specific Populations (8.1, 8.2)].

Encourage patients to enroll in the North American Antiepileptic Drug (NAAED) Pregnancy Registry if they become pregnant. This registry is collecting information about the safety of antiepileptic drugs during pregnancy [see Use in Specific Populations (8.1)].

This product's label may have been updated. For current full prescribing information, please visit www.pfizer.com.

LAB-0105-34.0

PRINCIPAL DISPLAY PANEL - 10 mL Vial Label

10 mL Single-dose Vial
NDC 0069-6001-10

Cerebyx®
(fosphenytoin sodium) Injection

500 mg PE/10 mL
(50 mg PE/mL)
(PE = phenytoin sodium equivalents)

For Intramuscular or Intravenous Use

PRINCIPAL DISPLAY PANEL - 10 mL Vial Package

10 Single-dose Vials (10 mL each)

NDC 0069-6001-21
Contains 10 of NDC 0069-6001-10

Cerebyx®
(fosphenytoin sodium) Injection

500 mg PE/10 mL
(50 mg PE/mL)
(PE = phenytoin sodium equivalents)

For Intramuscular or Intravenous Use

Pfizer Hospital

Rx only

PRINCIPAL DISPLAY PANEL - 2 mL Vial Label

2 mL Single-dose Vial
NDC 0069-6001-02

Cerebyx®
(fosphenytoin sodium) Injection

100 mg PE/2 mL
(50 mg PE/mL)

(PE = phenytoin sodium equivalents)

PRINCIPAL DISPLAY PANEL - 2 mL Vial Carton

25 Single-dose Vials (2 mL each)

NDC 0069-6001-25
Contains 25 of NDC 0069-6001-02

Cerebyx®
(fosphenytoin sodium) Injection

100 mg PE/2 mL
(50 mg PE/mL)

(PE = phenytoin sodium equivalents)

For Intramuscular or Intravenous Use

Pfizer Hospital

Rx only